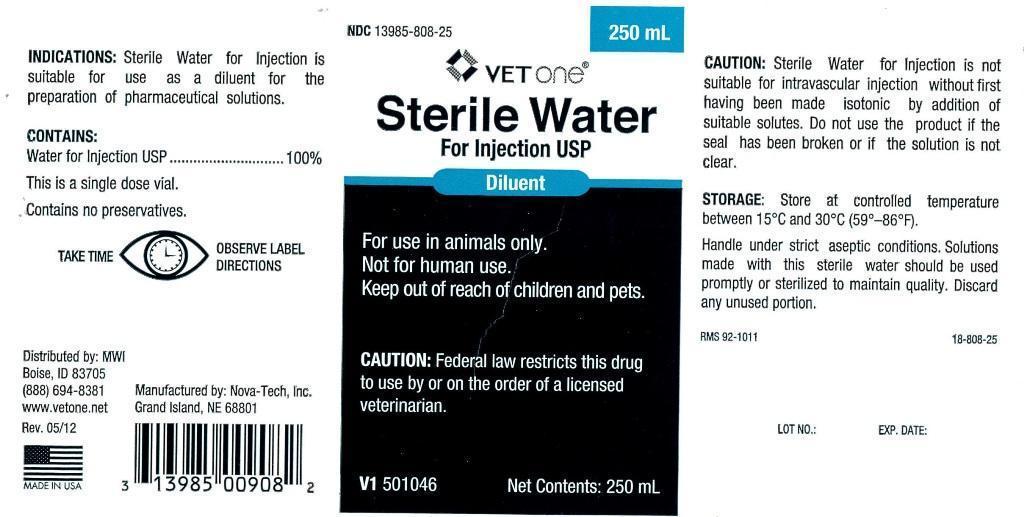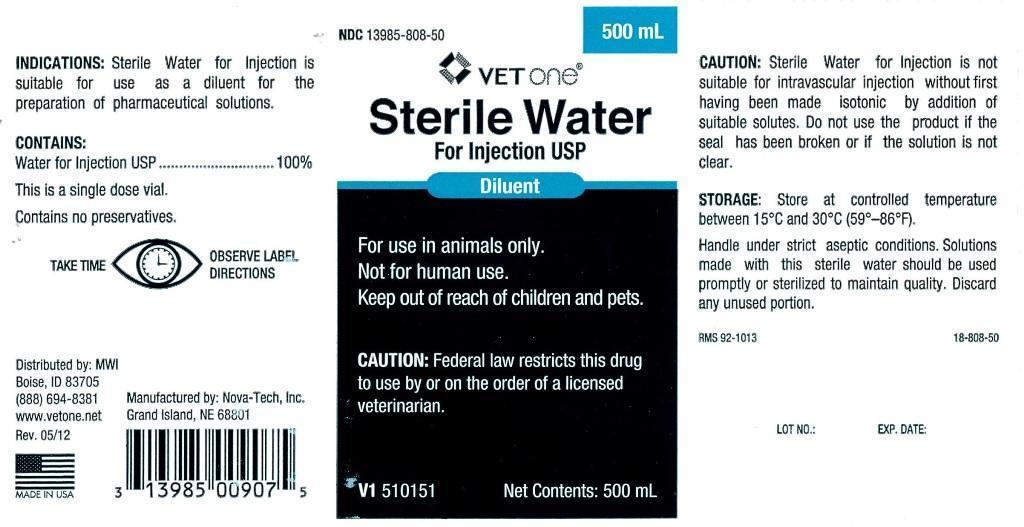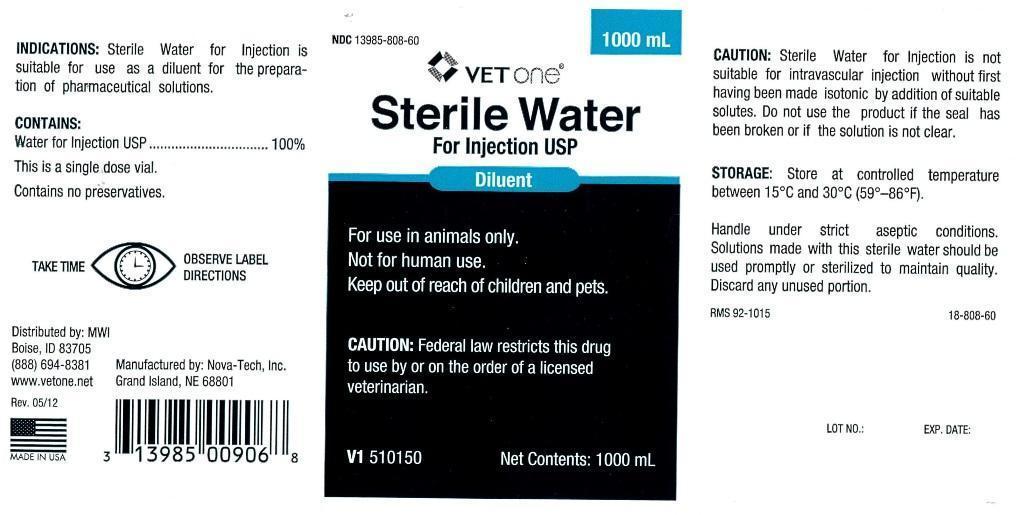 DRUG LABEL: Sterile Water
NDC: 13985-808 | Form: INJECTION
Manufacturer: MWI (VetOne)
Category: animal | Type: PRESCRIPTION ANIMAL DRUG LABEL
Date: 20140610

ACTIVE INGREDIENTS: WATER 250 mL/250 mL

Sterile Water For Injection USP

INDICATIONS:

Sterile Water for Injection is suitable for use as a diluent for the preparation of pharmaceutical solutions.

CONTAINS:

Water for Injection USP.............................100%

This is a single dose vial.

Contains no preservatives.

WARNINGS AND PRECAUTIONS

TAKE TIME OBSERVE LABEL DIRECTIONS

INFORMATION FOR OWNERS/CAREGIVERS

Distributed by: MWI
Boise, ID 83705
(888) 694-8381
www.vetone.net

Rev. 05/12

Manufactured by: Nova-Tech, Inc.
Grand Island, NE 68801

V1 501046

Net Contents: 250 mL

RMS 92-1011 18-808-25

LOT NO.: EXP. DATE:

VETERINARY INDICATIONS

For use in animals only.

Not for human use.

Keep out of reach of children and pets.

CAUTION:

Federal law restricts this drug to use by or on the order of a licensed veterinarian.

CAUTION:

Sterile water for Injection is not suitable for intravascular injection without first having been made isotonic by addition of suitable solutes. Do not use the product if the seal has been broken or if the solution is not clear.

STORAGE:

Store at controlled temperature between 15 degrees C and 30 degrees C (59 degrees - 86 degrees F).

Handle under strict aseptic conditions. Solutions made with this sterile water should be used promptly or sterilized to maintain quality. Discard any unused portion.